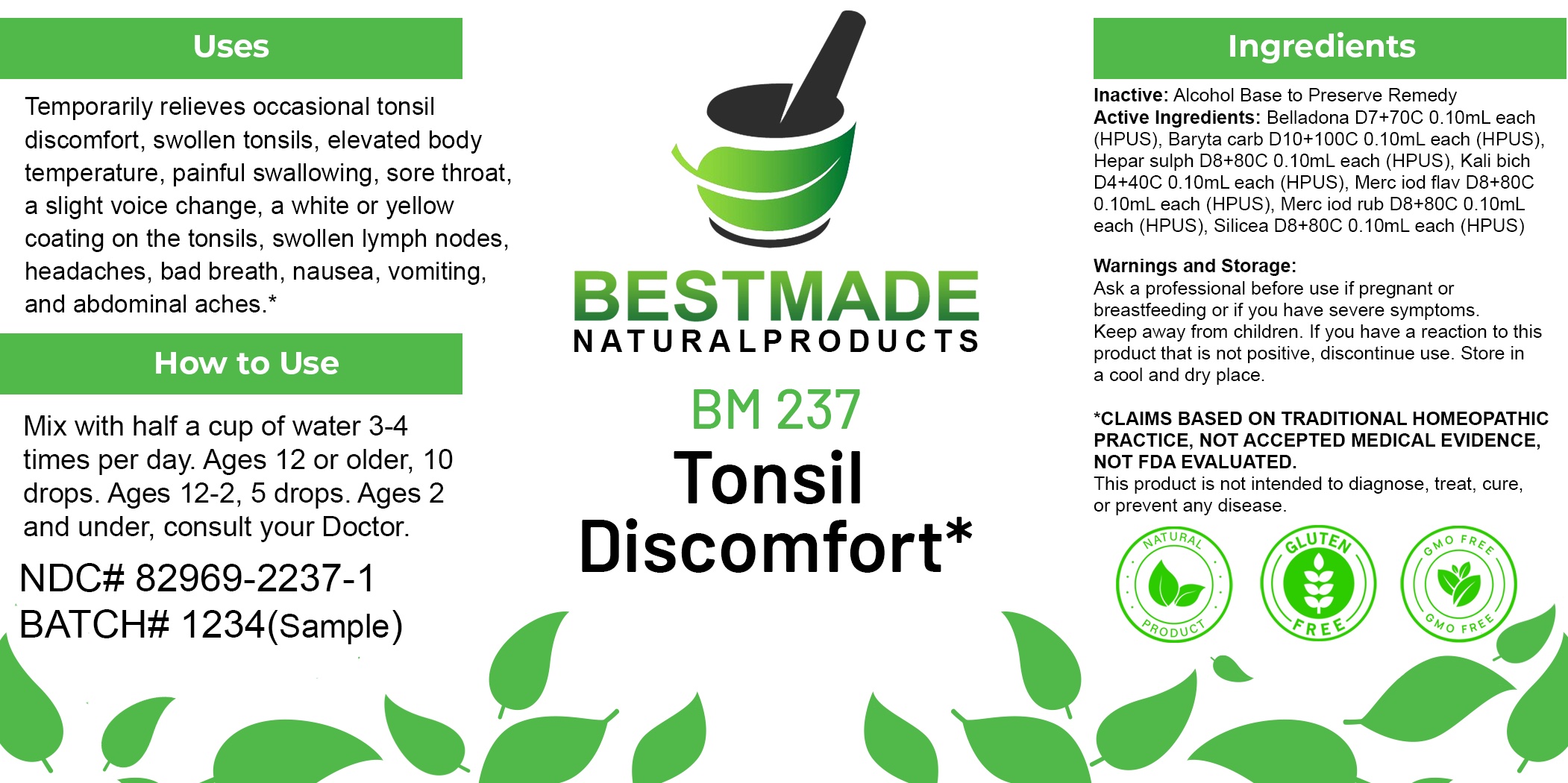 DRUG LABEL: Bestmade Natural Products BM237
NDC: 82969-2237 | Form: LIQUID
Manufacturer: Bestmade Natural Products
Category: homeopathic | Type: HUMAN OTC DRUG LABEL
Date: 20250304

ACTIVE INGREDIENTS: BARIUM CARBONATE 30 [hp_C]/30 [hp_C]; MERCUROUS IODIDE 30 [hp_C]/30 [hp_C]; CALCIUM SULFIDE 30 [hp_C]/30 [hp_C]; POTASSIUM DICHROMATE 30 [hp_C]/30 [hp_C]; MERCURIC IODIDE 30 [hp_C]/30 [hp_C]; ATROPA BELLADONNA 30 [hp_C]/30 [hp_C]; SILICA 30 [hp_C]/30 [hp_C]
INACTIVE INGREDIENTS: ALCOHOL 30 [hp_C]/30 [hp_C]

BM237

DOSAGE AND ADMINISTRATION

How to Use

Mix with half a cup of water 3-4 times per day. Ages 12 or older, 10 drops. Ages 12-2, 5 drops. Ages 2 and under, consult your Doctor.

Inactive:

Alcohol Base to Preserve Product

ACTIVE INGREDIENT

Active Ingredients: Belladona D7+70C 0.10mL each (HPUS), Baryta carb D10+100C 0.10mL each (HPUS), Hepar sulph D8+80C 0.10mL each (HPUS), Kali bich D4+40C 0.10mL each (HPUS), Merc iod flav D8+80C 0.10mL each (HPUS), Merc iod rub D8+80C 0.10mL each (HPUS), Silicea D8+80C 0.10mL each (HPUS)

KEEP OUT OF REACH OF CHILDREN

Warnings and Storage:

Ask a professional before use if pregnant or breastfeeding or if you have severe symptoms.

Keep away from children. If you have a reaction to this product that is not positive, discontinue use. Store in a cool and dry place

*CLAIMS BASED ON TRADITIONAL HOMEOPATHIC PRACTICE, NOT ACCEPTED MEDICAL EVIDENCE NOT FDA EVALUATED.
This product is not intended to diagnose, treat, cure, or prevent any disease.

Warnings and Storage:

Ask a professional before use if pregnant or breastfeeding or if you have severe symptoms.

Keep away from children. If you have a reaction to this product that is not positive, discontinue use. Store in a cool and dry place

*CLAIMS BASED ON TRADITIONAL HOMEOPATHIC PRACTICE, NOT ACCEPTED MEDICAL EVIDENCE NOT FDA EVALUATED.
This product is not intended to diagnose, treat, cure, or prevent any disease.

Uses
Temporarily relieves occasional tonsil discomfort, swollen tonsils, elevated body temperature, painful swallowing, sore throat, a slight voice change, a white or yellow coating on the tonsils, swollen lymph nodes, headaches, bad breath, nausea, vomiting, and abdominal aches.*

Uses
Temporarily relieves occasional tonsil discomfort, swollen tonsils, elevated body temperature, painful swallowing, sore throat, a slight voice change, a white or yellow coating on the tonsils, swollen lymph nodes, headaches, bad breath, nausea, vomiting, and abdominal aches.*

Entire package label